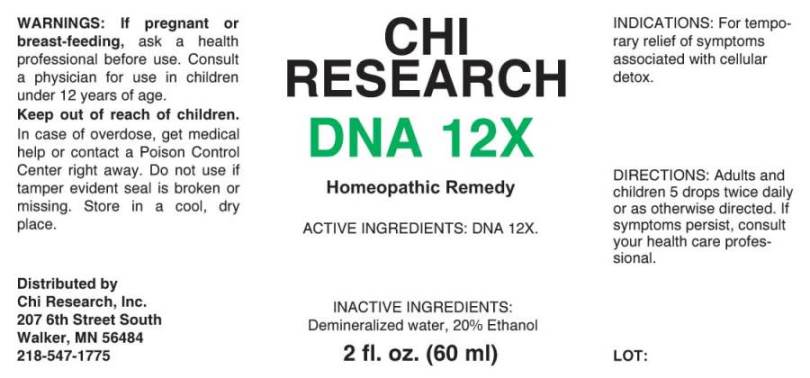 DRUG LABEL: DNA
NDC: 52654-0002 | Form: LIQUID
Manufacturer: Chi Research Inc
Category: homeopathic | Type: HUMAN OTC DRUG LABEL
Date: 20240712

ACTIVE INGREDIENTS: HERRING SPERM DNA 12 [hp_X]/1 mL
INACTIVE INGREDIENTS: WATER; ALCOHOL

DRUG FACTS:

ACTIVE INGREDIENTS:

DNA 12X.

INDICATIONS:

For temporary relief of symptoms associated with cellular detox.

WARNINGS:

If pregnant or breast feeding, ask a health professional before use. Consult a physician for use in children under 12 years of age.

Keep out of reach of children. In case of overdose, get medical help or contact a Poison Control Center right away.

Do not use if tamper evident seal is broken or missing. Store in cool, dry place.

DIRECTIONS:

Adults and children 5 drops twice daily or as otherwise directed. If symptoms persist, consult your health care professional.

INACTIVE INGREDIENTS:

Demineralized water, 20% Ethanol.

KEEP OUT OF REACH OF CHILDREN:

In case of overdose, get medical help or contact a Poison Control Center right away.

INDICATIONS:

For temporary relief of symptoms associated with cellular detox.

QUESTIONS:

Distributed by

Chi Research, Inc.

207 6th Street South

Walker, MN 56484

218-547-1775

PACKAGE LABEL DISPLAY:

CHI

RESEARCH

DNA 12X

Homeopathic Remedy

2 fl. oz. (60 ml)